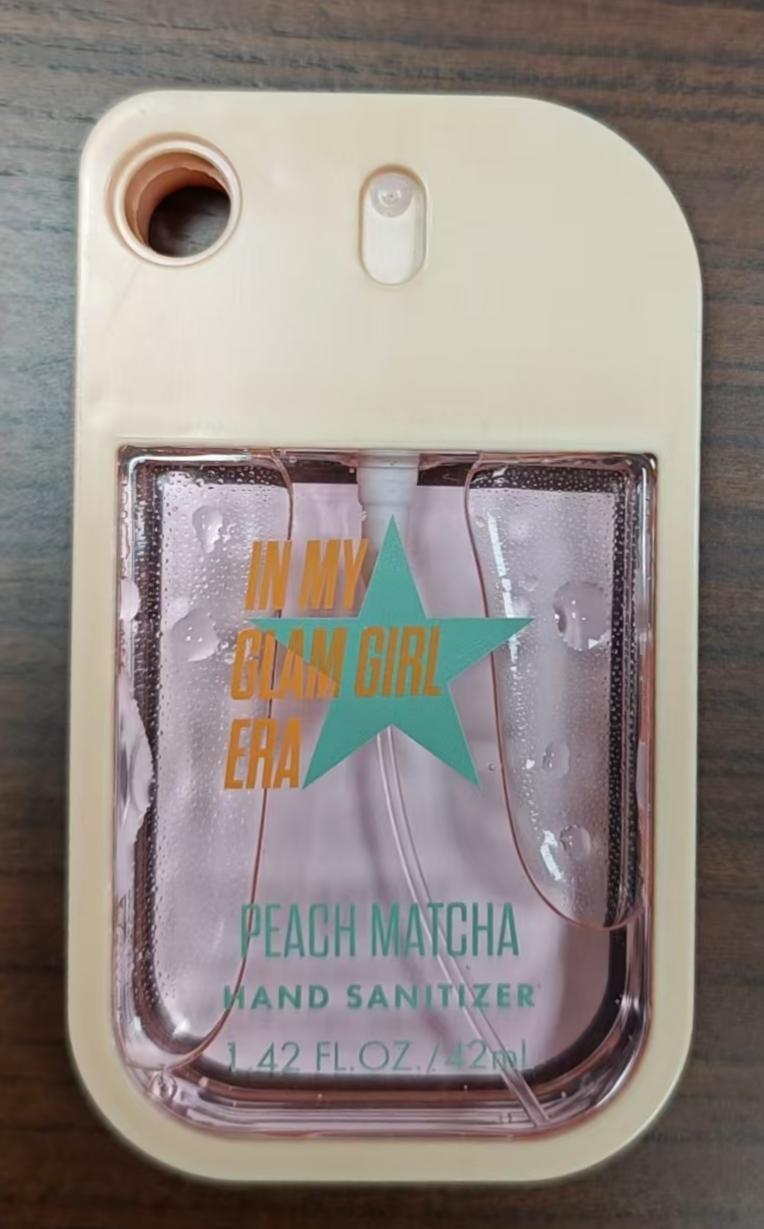 DRUG LABEL: palm party
NDC: 87322-1169 | Form: SPRAY
Manufacturer: Dongyang Loulee Cosmetics Co.,Ltd.
Category: otc | Type: HUMAN OTC DRUG LABEL
Date: 20260115

ACTIVE INGREDIENTS: ALCOHOL 60 mL/100 mL
INACTIVE INGREDIENTS: WATER 39.776 mL/100 mL; ACID RED 18 0.024 mL/100 mL; FRAGRANCE 13576 0.2 mL/100 mL

Active ingredient(s)

Alcohol 60%

Purpose(s)

Antiseptic

Uses

- To help reduce bacteria on the skin.
- Recommended for repeated use.

Warnings

For external use only. Flammable. Keep away from fire or flame.

When using this product

Do not use in or near the eyes. In case of contact, rinse eyes thoroughly with water.

Stop use and ask a doctor if

Irritation or rash appears and lasts.

Keep out of reach of children

If swallowed, get medical help or contact a Poison Control Center right away.

Directions

- Spray an adequate amount into your palm to fully coat your hands.
- Rub your hands together thoroughly until dry.
- Supervise children under 6 years of age when using this product to avoid swallowing.

Other information

- Store at 20℃ to 25℃ (68℉ to 77℉).
- May discolor certain fabrics or surfaces.

Inactive ingredients

WATER, FRAGRANCE, ACID RED 18

Questions or comments?

213-396-1046 / MalachiPerez291@gmail.com

Box Front Panel

IN MY GLAM GIRL ERA

PEACH MATCHA
HAND SANITIZER